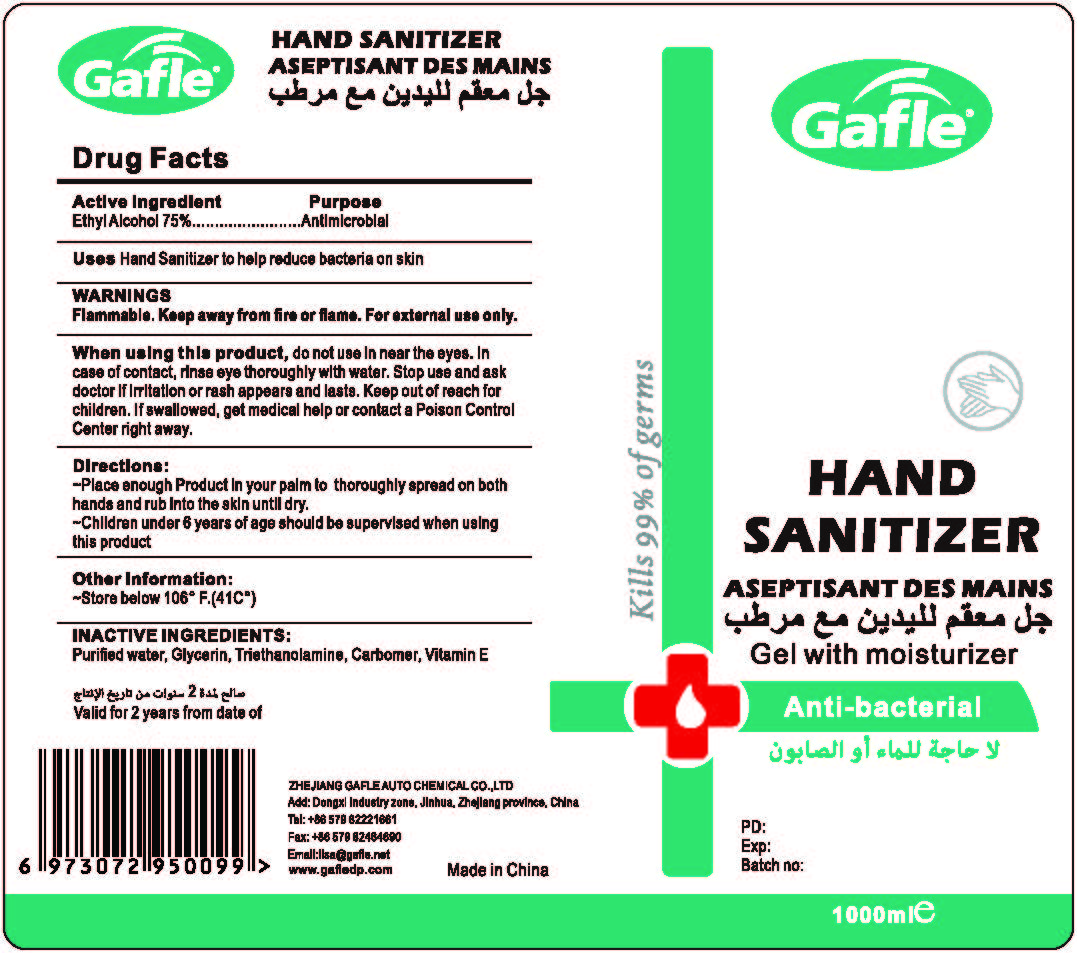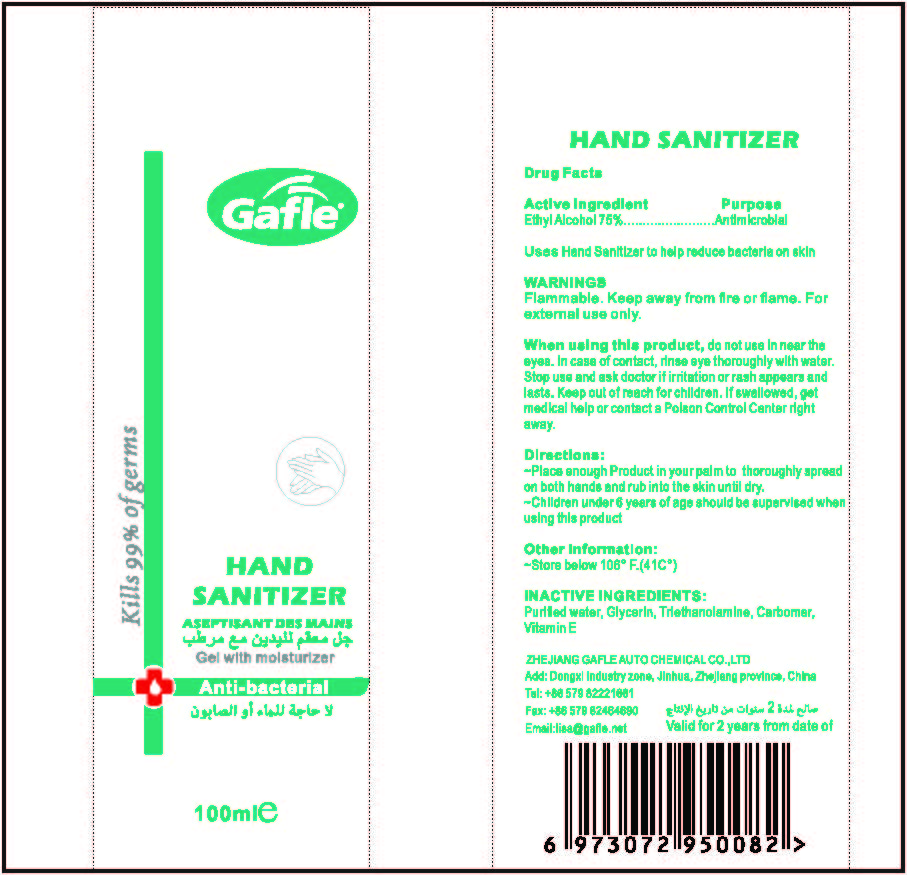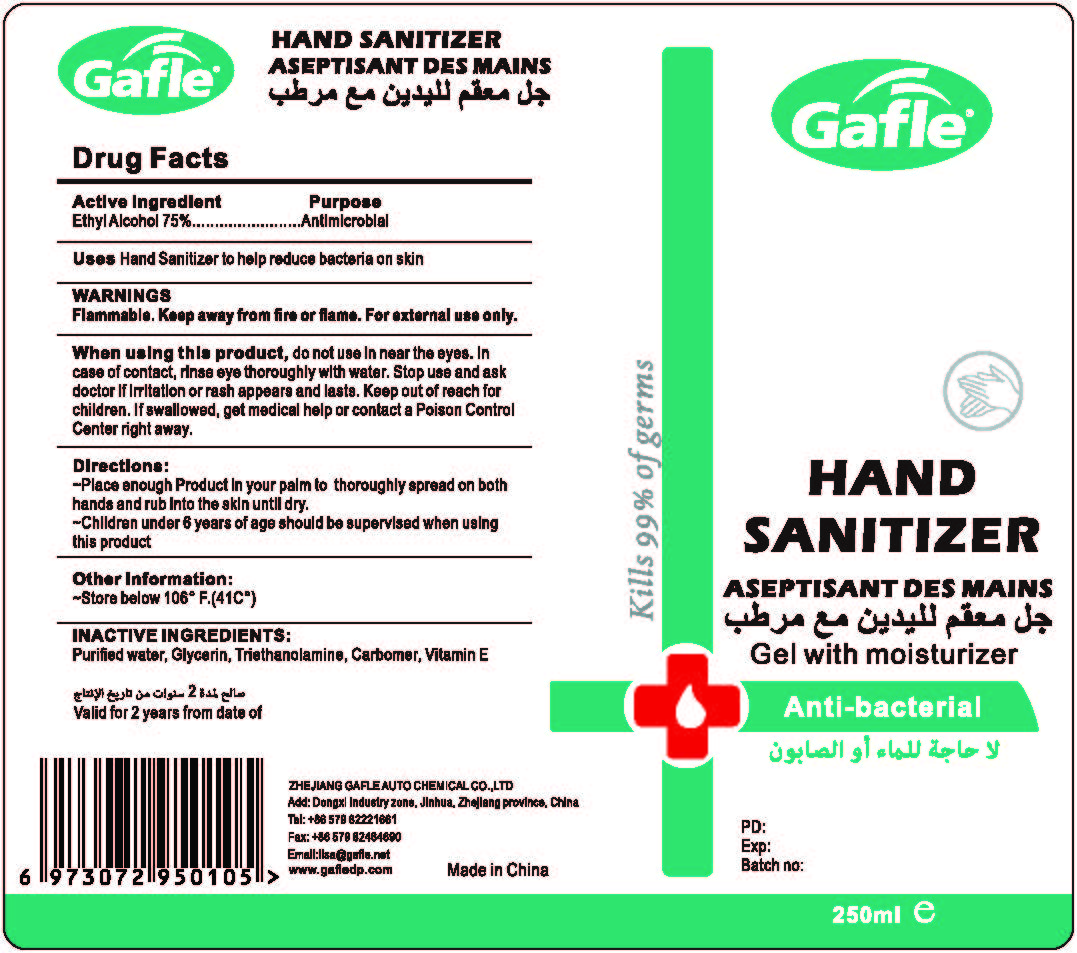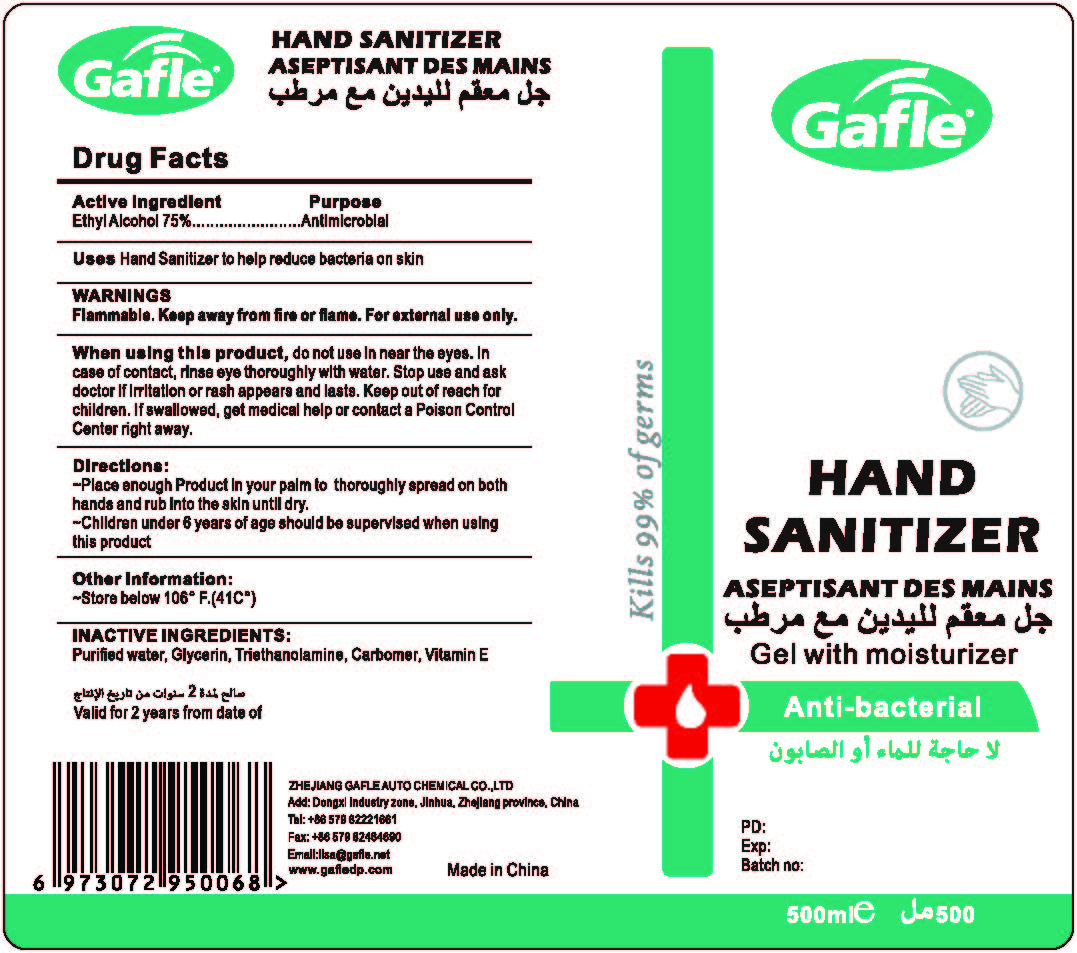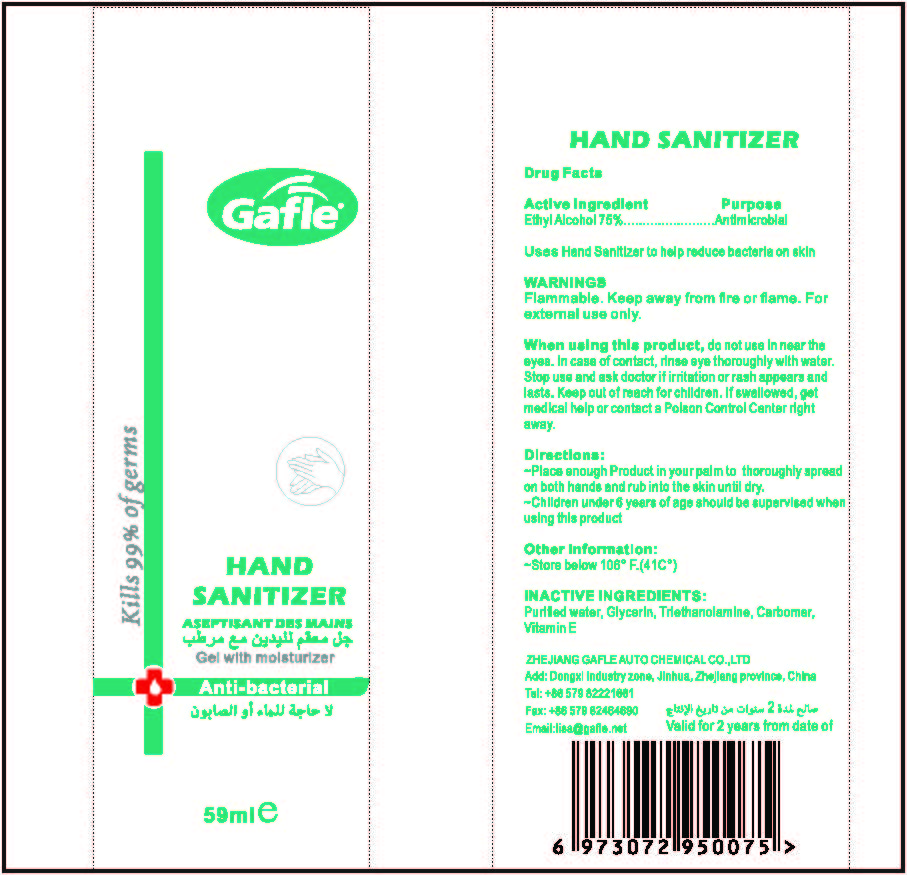 DRUG LABEL: Hand Sanitizer
NDC: 74763-001 | Form: GEL
Manufacturer: Zhejiang Gafle Auto Chemical Co., Ltd.
Category: otc | Type: HUMAN OTC DRUG LABEL
Date: 20220328

ACTIVE INGREDIENTS: ALCOHOL 75 mL/100 mL
INACTIVE INGREDIENTS: GLYCERIN; TROLAMINE; CARBOMER HOMOPOLYMER, UNSPECIFIED TYPE; .ALPHA.-TOCOPHEROL; WATER

001

Active Ingredient

Ethyl Alcohol 75%

Purpose

Antimicrobial

Uses

Hand Sanitizer to help reduce bacteria on skin

WARNINGS

Flammable. Keep away from fire or flame. For external use only.

When using this product

do not use in near the eyes. In case of contact, rinse eye thoroughly with water. Stop use and ask doctor if irritation or rash appears and lasts. Keep out of reach for children. If swallowed, get medical help or contact a Poison Control Center right away.

Directions

Place enough Product in your palm to thoroughly spread on both hands and rub into the skin until dry.

Children under 6 years of age should be supervised when using this product.

Other information

Store below 106° F.(41C°)

Inactive ingredients

Purified water, Glycerin, Triethanolamine, Carbomer, Vitamin E